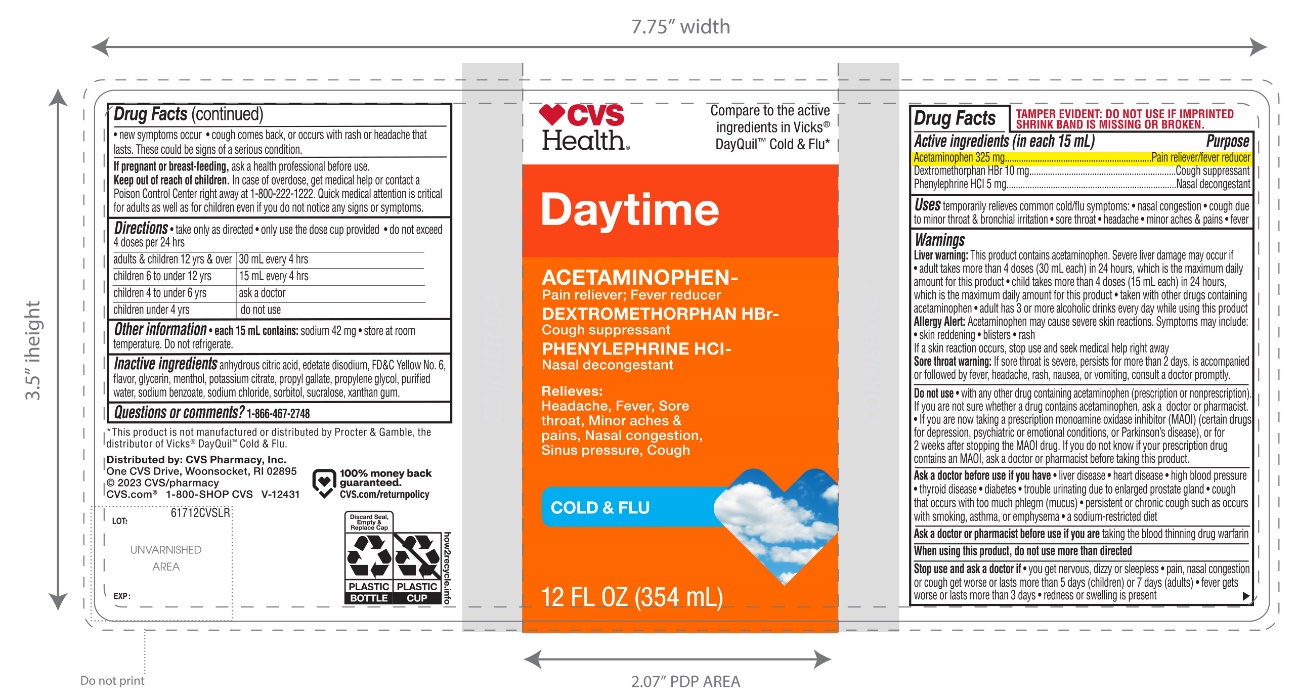 DRUG LABEL: Daytime Cold and Flu Relief
NDC: 51316-617 | Form: LIQUID
Manufacturer: CVS PHARMACY
Category: otc | Type: HUMAN OTC DRUG LABEL
Date: 20251208

ACTIVE INGREDIENTS: ACETAMINOPHEN 325 mg/15 mL; DEXTROMETHORPHAN HYDROBROMIDE 10 mg/15 mL; PHENYLEPHRINE HYDROCHLORIDE 5 mg/15 mL
INACTIVE INGREDIENTS: ANHYDROUS CITRIC ACID; EDETATE DISODIUM; FD&C YELLOW NO. 6; GLYCERIN; MENTHOL, UNSPECIFIED FORM; POTASSIUM CITRATE ANHYDROUS; PROPYL GALLATE; PROPYLENE GLYCOL; WATER; SODIUM BENZOATE; SODIUM CHLORIDE; SORBITOL; SUCRALOSE; XANTHAN GUM

CVS DayTime Severe Cold and Flu Relief

Active ingredients (in each 15 mL)

Acetaminophen 325 mg

Dextromethorphan HBr 10 mg

Phenylephrine HCl 5 mg

Purposes

Pain reliever/fever reducer

Cough suppressant

Nasal decongestant

Uses

- temporarily relieves common cold/flu symptoms:
  - nasal congestion
  - cough due to minor throat and bronchial irritation
  - minor aches and pains
  - headache
  - fever
  - sore throat

Warnings

Liver warning:This product contains acetaminophen. Severe liver damage may occur if

- adult takes more than 4 doses (30 mL) in 24 hrs which is maximum daily amount for this product
- child takes more than 4 doses (15 mL) in 24 hours, which is the maximum daily amount for this product
- taken with other drugs containing acetaminophen
- adult has 3 or more alcoholic drinks every day while using this product

Allergy alert: Acetaminophen may cause severe skin reactions. Symptoms may include:

- Skin reddening
- Blisters
- Rash

If a skin reaction occurs, stop use and seek medical help right away.

Sore throat warning:If sore throat is severe, persists for more than 2 days, is accompanied or followed by fever, headache, rash, nausea, or vomiting, consult a doctor promptly.

Do not use

- with any other drug containing acetaminophen (prescription or non-prescription). If you are not sure whether a drug contains acetaminophen, ask a doctor or pharmacist.
- if you are now taking a prescription monoamine oxidase inhibitor (MAOI) (certain drugs for depression, psychiatric or emotional conditions, or Parkinson's disease) or for 2 weeks after stopping the MAOI drug. If you do not know if your prescription drug contains an MAOI, ask a doctor or pharmacist before taking this product.

Ask a doctor before use if you have

- liver disease
- heart disease
- high blood pressure
- thyroid disease
- diabetes
- trouble urinating due to an enlarged prostate gland
- cough that occurs with too much phlegm (mucus)
- persistent or chronic cough such as occurs with smoking, asthma, or emphysema
- a sodium-restricted diet

Ask a doctor or pharmacist before use if you are

taking the blood thinning drug warfarin.

When using this product,

do not use more than directed.

Stop use and ask a doctor if

- you get nervous, dizzy, or sleepless
- pain, nasal congestion or cough gets worse, or lasts more than 5 days (children) or 7 days (adults)
- fever gets worse or lasts more than 3 days
- redness or swelling is present
- new symptoms occur
- cough comes back or occurs with a rash or headache that lasts. These could be signs of a serious condition.

If pregnant or breast-feeding,

ask a health professional before use.

Keep out of reach of children.

In case of overdose, get medical help or contact a Poison Control Center (1-800-222-1222) right away. Quick medical attention is critical for adults as well as for children even if you do not notice any signs or symptoms.

Directions

- take only as directed
- only use the dose cup provided
- do not exceed 4 doses per 24 hours

Adults & children 12 yrs & over | 30 mL every 4 hrs.
Children 6 to under 12 yrs | 15 mL every 4 hrs
Children 4 to under 6 yrs | Ask a doctor
Children under 4 yrs. | Do not use

Other information

- each 15 mL contains: sodium 42 mg
- store at room temperature. Do not refrigerate

Inactive ingredients

Anhydrous citric acid, disodium edetate, FD&C Yellow No 6, flavors, glycerin, menthol, potassium citrate, propyl gallate, propylene glycol, purified water, sodium benzoate, sodium chloride, sorbitol, sucralose, xanthan gum

Questions or comments?

1-866-467-2748

Principal Display Panel

Compare tothe active ingredients in VICKS® Dayquil™ Cold & Flu*

NDC 51316-617-12

Day Time

Cold & Flu Relief

Acetaminophen,Phenylephrine HCI,

Dextromethorphan HBr

For Relieves of

- Headache, Fever, Sore Throat, Minor Aches & Pains
- Nasal congestion & Sinus Pressure
- Cough

12 FL OZ (354 mL)

DO NOT USE IF IMPRINTED SHRINK BAND IS MISSING OR BROKEN

Distributed by:

*This product.is not manufactured or distributed by Procter & Gamble, distributer of Vicks® Dayquil™ Cold & Flu.